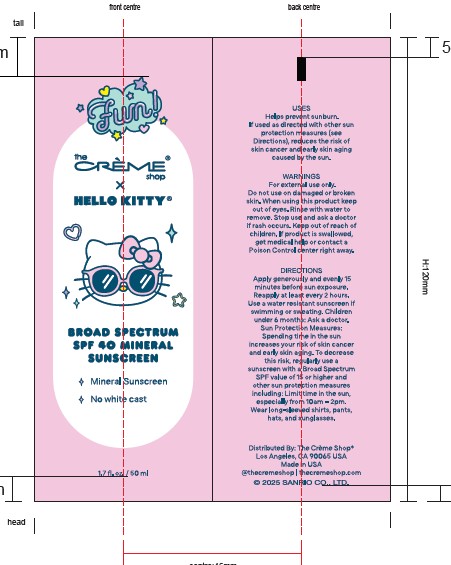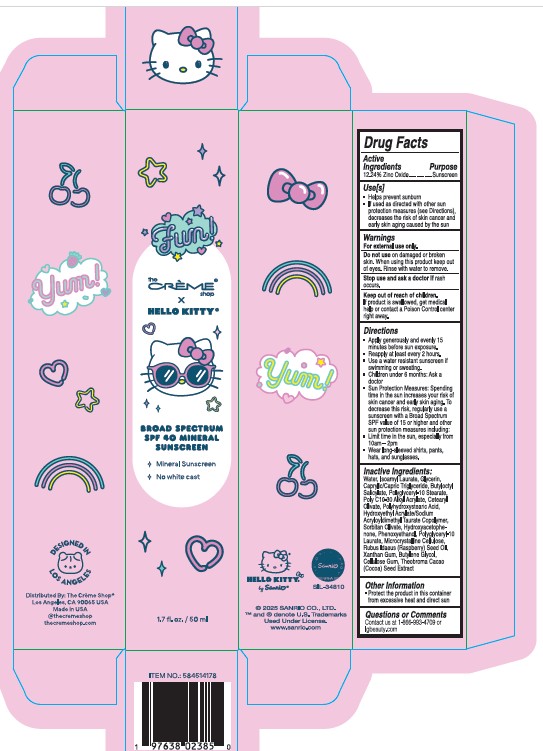 DRUG LABEL: Hello Kitty Fun Broad Spectrum SPF 40
NDC: 81123-331 | Form: CREAM
Manufacturer: The Creme Shop Inc
Category: otc | Type: HUMAN OTC DRUG LABEL
Date: 20250321

ACTIVE INGREDIENTS: ZINC OXIDE 12.24 mg/100 mL
INACTIVE INGREDIENTS: BUTYLOCTYL SALICYLATE; POLYGLYCERYL-10 STEARATE; PHENOXYETHANOL; POLYHYDROXYSTEARIC ACID (2300 MW); BEHENYL ACRYLATE POLYMER; POLYGLYCERYL-10 LAURATE; MICROCRYSTALLINE CELLULOSE; RUBUS IDAEUS (RASPBERRY) SEED OIL; WATER; CELLULOSE GUM; SORBITAN OLIVATE; XANTHAN GUM; CAPRYLIC/CAPRIC TRIGLYCERIDE; BUTYLENE GLYCOL; GLYCERIN; CETEARYL OLIVATE; HYDROXYETHYL ACRYLATE/SODIUM ACRYLOYLDIMETHYL TAURATE COPOLYMER (45000 MPA.S AT 1%); HYDROXYACETOPHENONE; COCOA; ISOAMYL LAURATE

The Crème Shop Hello Kitty Fun Broad Spectrum SPF 40

Active Ingredient

Zinc Oxide 12.24%

Purpose
Sunscreen

USES

- Helps prevent sunburn
- If used as directed with other sun protection measures (see Directions), decreases the risk of skin cancer and early skin aging caused by the sun

Warnings
For external use only.

Do not use on damaged or broken skin. When using this product keep out of eyes. Rinse with water to remove.

Stop use and ask a doctor if rash occurs.

Keep out of reach of children. If product is swallowed, get medical help or contact a Poison Control center right away.

DIRECTIONS

- Apply generously and evenly 15 minutes before sun exposure.
- Reapply at least every 2 hours
- Use a water resistant sunscreen if swimming or sweating.
- Children under 6 months: Ask a doctor.
- Sun Protection Measures: Spending time in the sun increases your risk of skin cancer and early skin aging. To decrease this risk, regularly use a sunscreen with a Broad Spectrum SPF value of 15 or higher and other sun protection measures including:
- Limit time in the sun, especially from 10am-2pm
- Wear long-sleeved shirts, pants, hats, and sunglasses.

Inactive Ingredients:
Water, Isoamyl Laurate, Glycerin,Caprylic/Capric Triglyceride, Butyloctyl Salicylate, Polyglyceryl-10 Stearate, Poly C10-30 Alkyl Acrylate, Cetearyl Olivate, Polyhydroxystearic Acid, Hydroxyethyl Acrylate/ Sodium Acryloyldimethyl Taurate Copolymer, Sorbitan Olivate, Hydroxyacetophenone, Phenoxyethanol, Polyglyceryl-10 Laurate, Microcrystalline Cellulose, Rubus Idaeus (Raspberry) Seed Oil, Xanthan Gum, Butylene Glycol, Cellulose Gum, Theobroma Cacao (Cocoa) Seed Extract.

OTHER INFORMATION

- Protect the product in this container from excessive heat and direct sun

QUESTIONS OR COMMENTS

Contact us at 1-866-993-4709 or lgbeauty.com